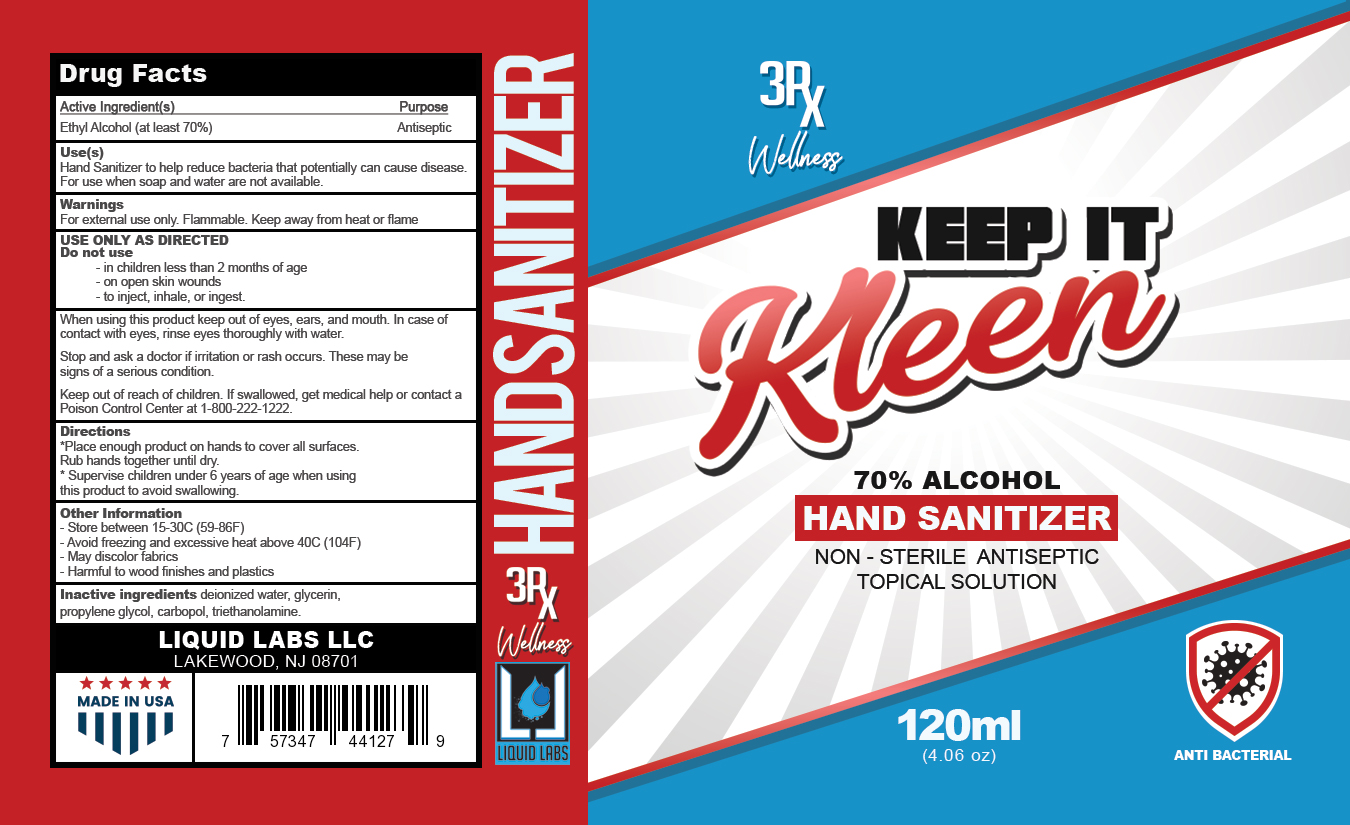 DRUG LABEL: KEEP IT KLEEN
NDC: 77568-123 | Form: GEL
Manufacturer: LIQUID LABS LLC
Category: otc | Type: HUMAN OTC DRUG LABEL
Date: 20220203

ACTIVE INGREDIENTS: ALCOHOL 70 mL/70 mL
INACTIVE INGREDIENTS: WATER; GLYCERIN

KEEP IT KLEEN

Active Ingredient

Ethyl Alcohol (at least 70%)

OTC - Purpose

ANTIMICROBIAL

Indications and Usage

HAND SANITIZER TO HELP REDUCE BACTERIA THAT POTENTIALLY CAN CAUSE DISEASE. FOR USE WHEN SOAP AND WATER ARE NOT AVAILABLE. FOR EXTERNAL USE ONLY. FLAMMABLE. KEEP AWAY FROM HEAT OR FLAM. DO NOT USE IN CHILDREN LESS THAN 2 MONTHS OF AGE OR ON OPEN SKIN WOUNDS

Warnings

Warnings: For external use onLy. Flammable. Keep away from heat or flame.

Purpose Uses (s)

Purpose: Antiseptic

Use(s) Hand Sanitizer to help reduce bacteria that potentially can cause disease. For use when soap and water not available.

USE ONLY AS DIRECTED

Do not use: in children less than 2 months of age

on open skin wounds

to inject, inhale, or ingest

When using this product keep out of eyes, ears, and mouth. In case of contact with eyes, rinse eyes throughly with water.

Stop and ask a doctor if irritation or rash occurs. These may be signs of a serious condition.

Keep our of reach of children. If swallowed, get medical help or contact a Poison Control Center at 1-800-222-1222

Directions

* Place enought product on hands to cover all surfaces.

Rub hands together until dry.

*Supervise children under 6 years of age when using this product to avoid swallowing

Dosage & Administration

DOSAGE FOR IS GEL. Route of Administration is TOPICAL; strength is Alcohol 70ML in 100 ML

USE ONLY AS DIRECTED

Do not use: in children less than 2 months of age

on open skin wounds

to inject, inhale, or ingest

When using this product keep out of eyes, ears, and mouth. In case of contact with eyes, rinse eyes throughly with water.

Stop and ask a doctor if irritation or rash occurs. These may be signs of a serious condition.

Keep our of reach of children. If swallowed, get medical help or contact a Poison Control Center at 1-800-222-1222

Directions

* Place enought product on hands to cover all surfaces.

Rub hands together until dry.

*Supervise children under 6 years of age when using this product to avoid swallowing

OTC - Keep Out of Reach of Children

KEEP OUT OF REACH OF CHILDREN. IF SWALLOWED, GET MEDICAL ATTENTION OR POISON CONTROL CENTER RIGHT AWAY.

Other Information

-Store between 15-30C (59-86F)

-Avoid freezing and excessive heat above 40C (104F)

-May discolor fabrics

-Harmful to wood finishes and plastics

Inactive Ingredients

Inactive ingredients deionized water, glycerin, propylene glycol, carbopol, triethanolamine.